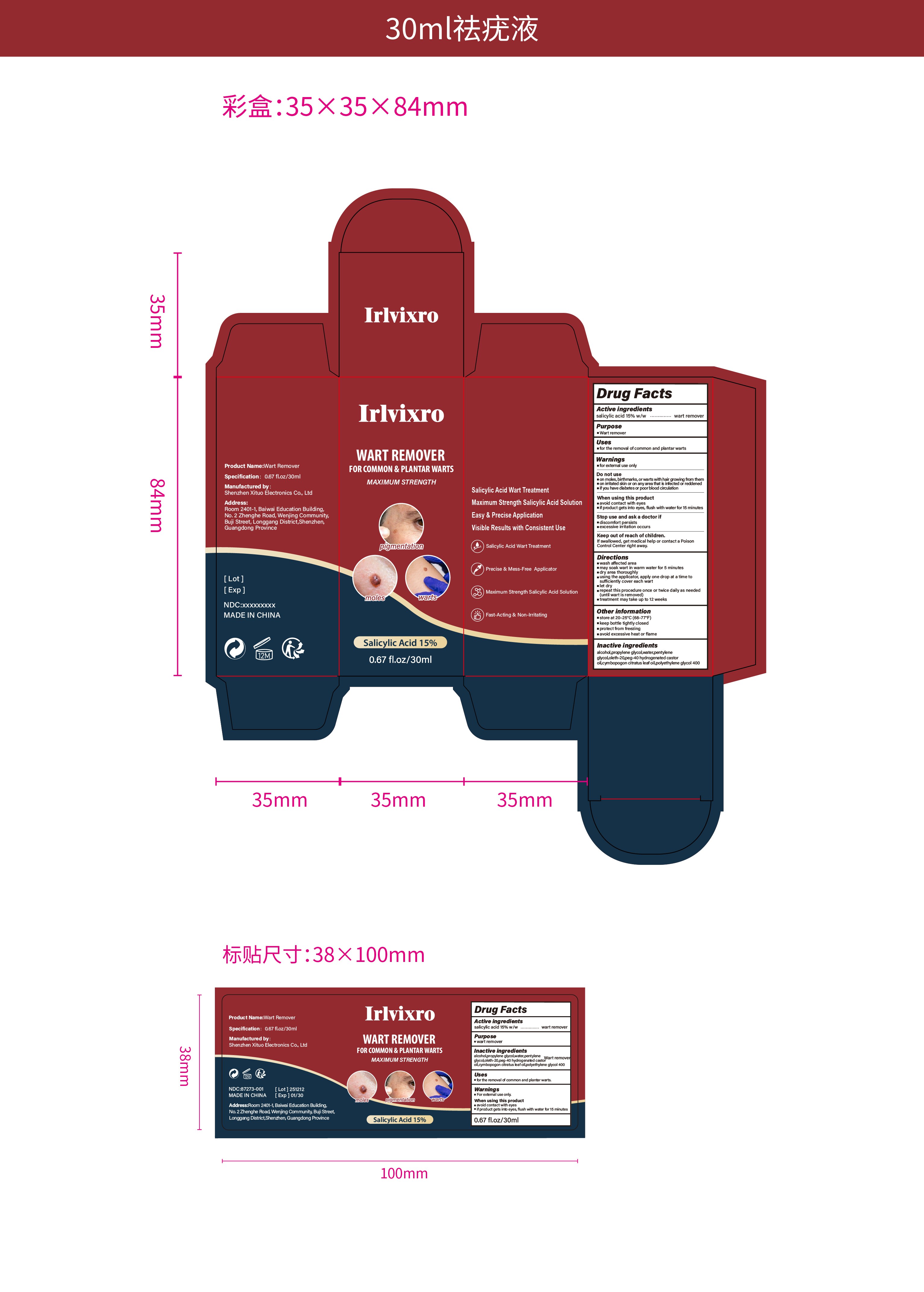 DRUG LABEL: Irlvixro WART REMOVER FOR COMMON PLANTAR WARTS
NDC: 87273-002 | Form: LIQUID
Manufacturer: Shenzhen Xituo Electronics Co., Ltd
Category: otc | Type: HUMAN OTC DRUG LABEL
Date: 20251226

ACTIVE INGREDIENTS: SALICYLIC ACID 15 g/100 mL
INACTIVE INGREDIENTS: WATER; PEG-40 HYDROGENATED CASTOR OIL; OLETH-20; ALCOHOL; POLYETHYLENE GLYCOL 400; CYMBOPOGON CITRATUS LEAF OIL; PROPYLENE GLYCOL; PENTYLENE GLYCOL

87273-002

Active Ingredient

salicylic acid 15%

Purpose

Wart remover

Use

for the removal ofcommon and plantar warts

Warnings

for external use only

Do not use

on moles, birthmarks, or warts with hair growing from them
on irritated skin or on any area that is infected or reddened
if you have diabetes or poor blood circulation

When Using

avoid contact with eyes
if product gets into eyes, flush with water for 15 minutes

Stop Use

discomfort persists
excessive irritation occurs

Ask Doctor

discomfort persists
excessive irritation occurs

Keep Out Of Reach Of Children

If swallowed, get medical help or contact a Poison Control Center right away.

Directions

wash affected area
may soak wart in warm water for 5 minutes
dry area thoroughly
using the applicator, apply one drop at a time to sufficiently cover each wart
let dry
repeat this procedure once or twice daily as needed (until wart is removed)
treatment may take up to 12 weeks

Other information

store at 20–25°C (68–77°F)
keep bottle tightly closed
protect from freezing
avoid excessive heat or flame

Inactive ingredients

ALCOHOL, PROPYLENE GLYCOL, WATER, PENTYLENE GLYCOL, OLETH-20, PEG-40 HYDROGENATED CASTOR OIL
CYMBOPOGON CITRATUS LEAF OIL, POLYETHYLENE GLYCOL 400